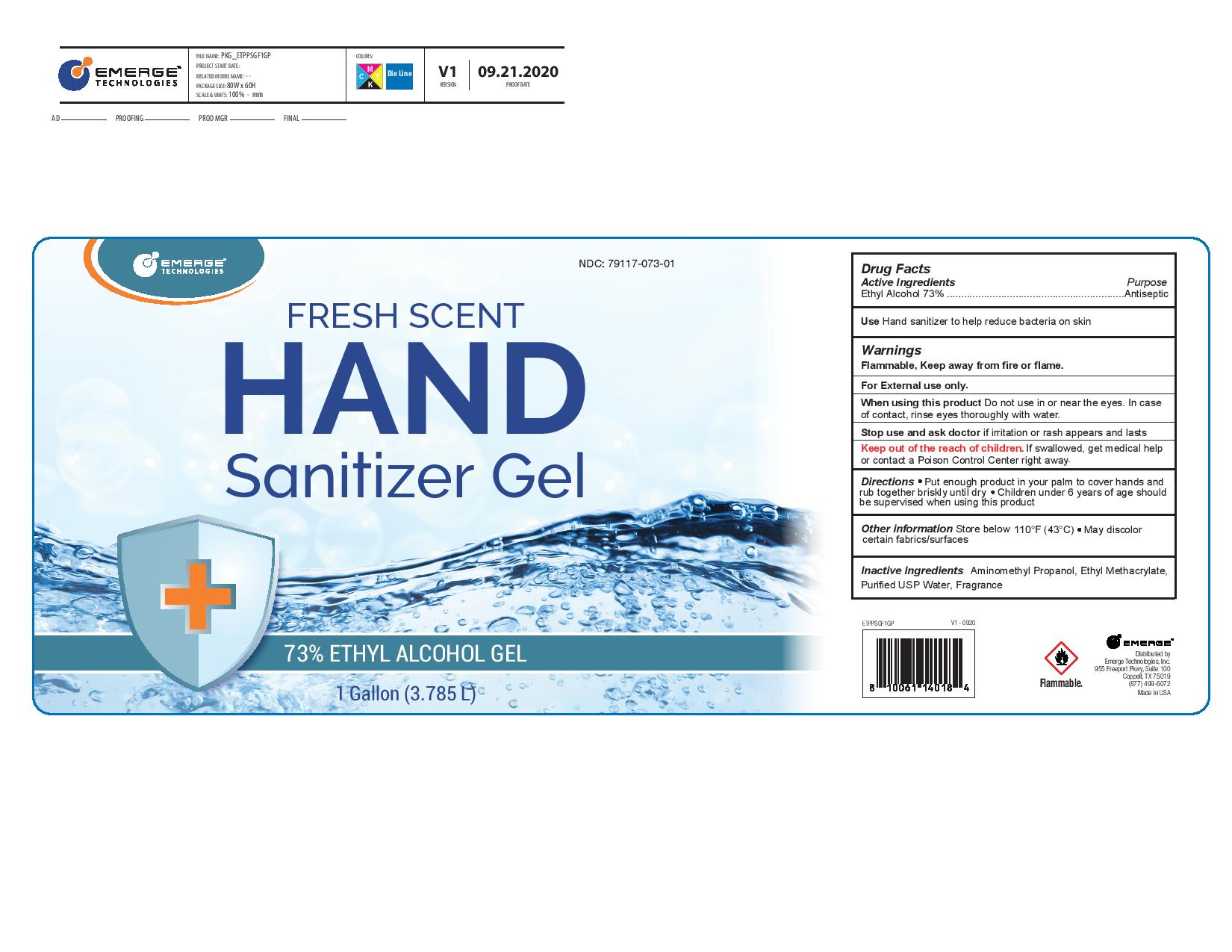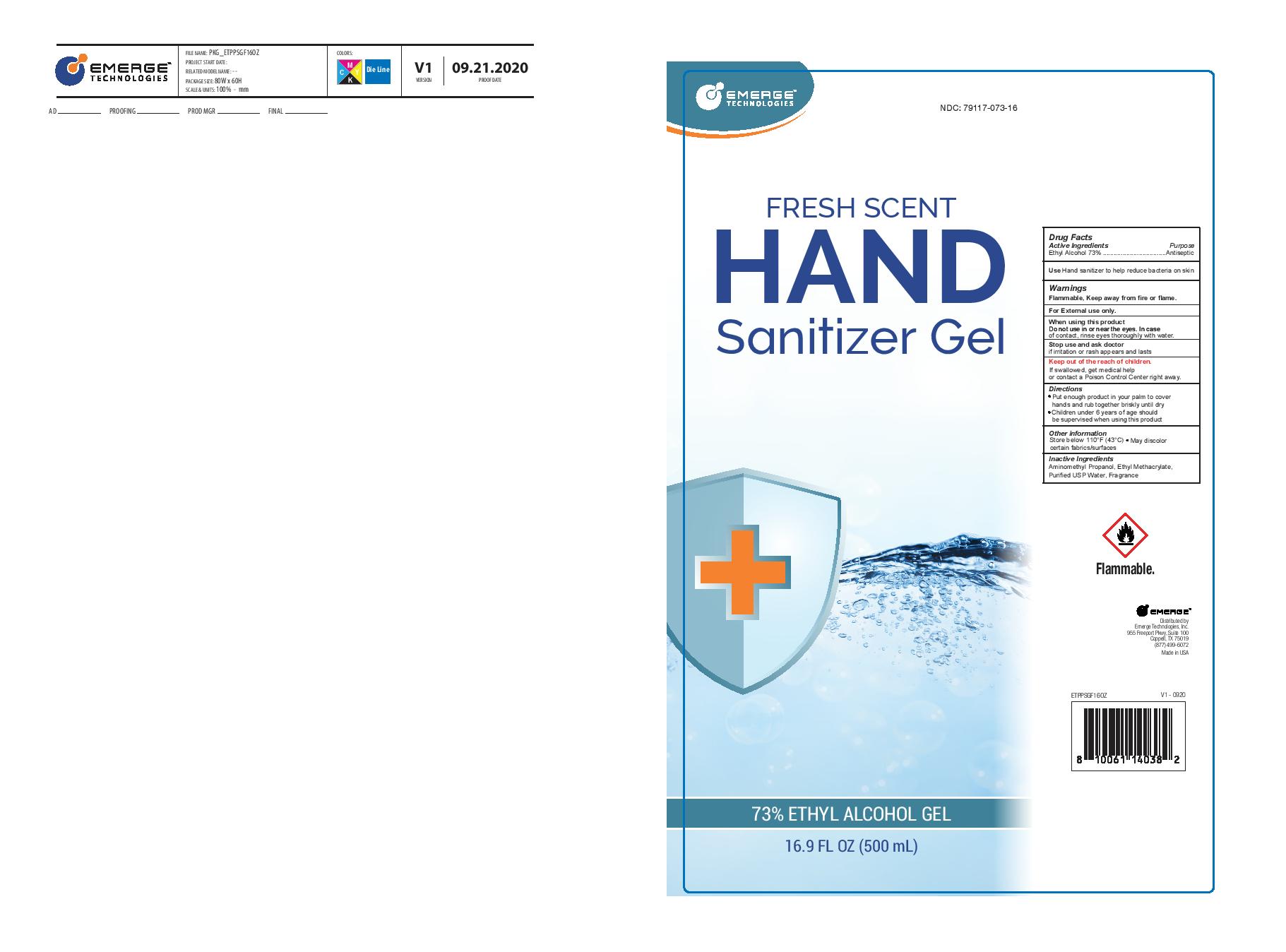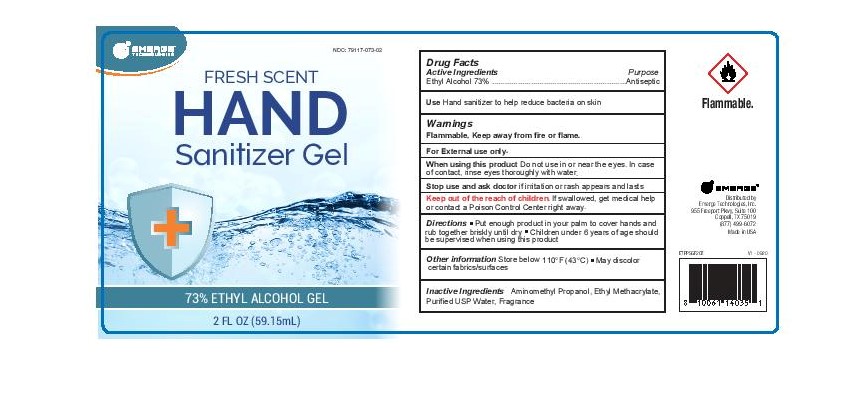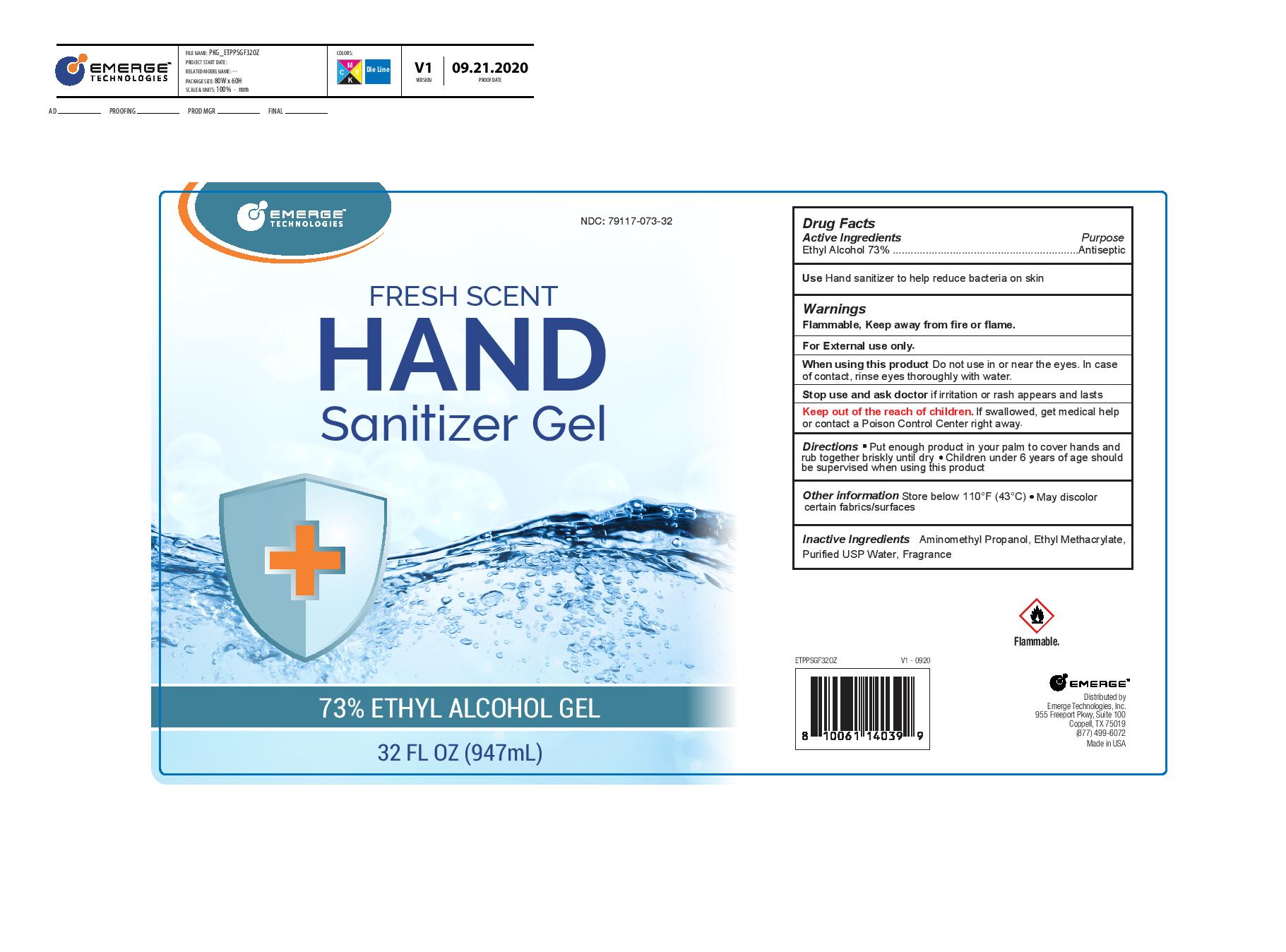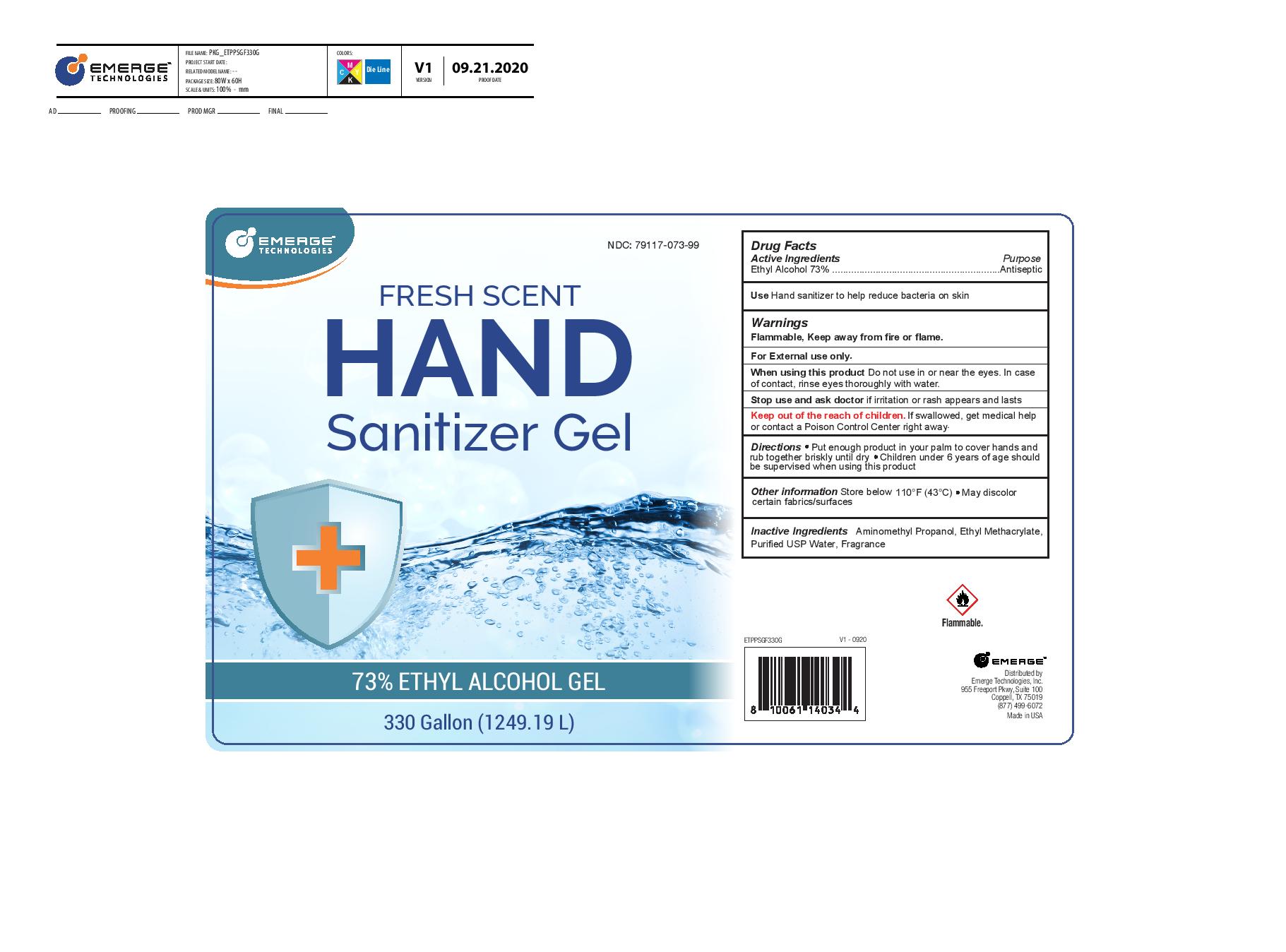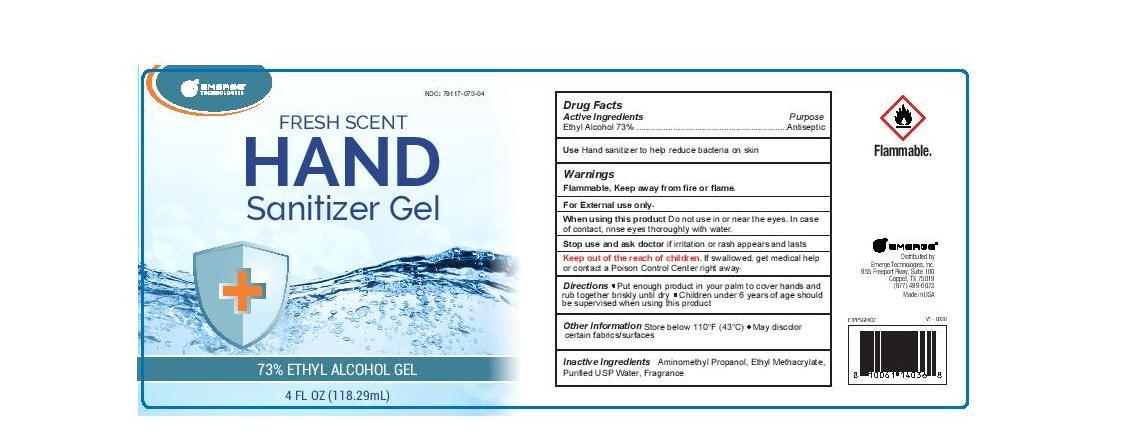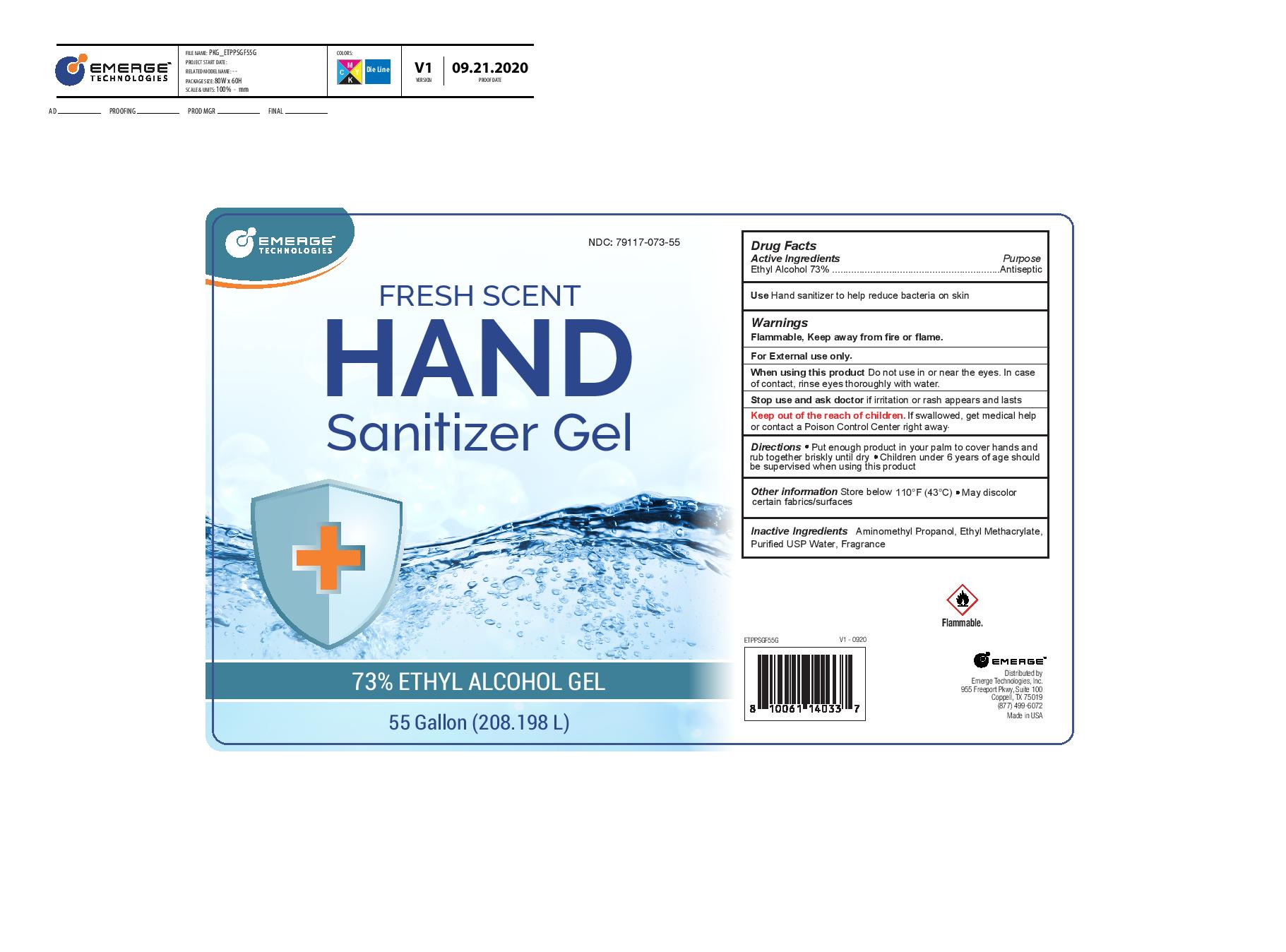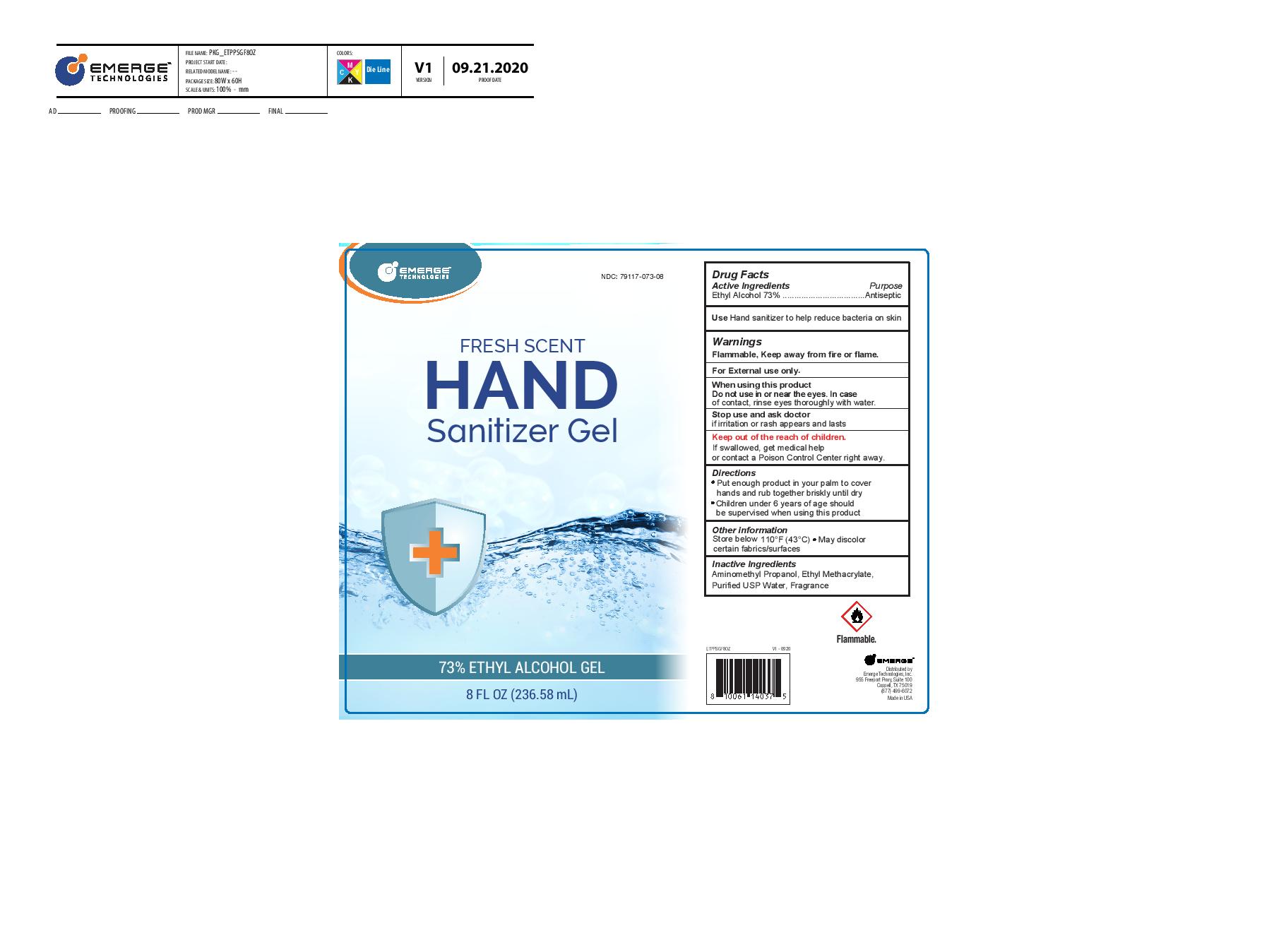 DRUG LABEL: Hand Sanitizer
NDC: 79117-073 | Form: GEL
Manufacturer: Emerge Technologies, Inc.
Category: otc | Type: HUMAN OTC DRUG LABEL
Date: 20200921

ACTIVE INGREDIENTS: ALCOHOL 73 mL/100 mL
INACTIVE INGREDIENTS: ETHYL METHACRYLATE; AMINOMETHYLPROPANOL; WATER

Emerge 73 % Alcohol- Fresh Scent

Active Ingredient(s)

Ethyl Alcohol 73% v/v. Purpose: Antiseptic

Purpose

Antiseptic, Hand Sanitizer

Use

Hand Sanitizer to help reduce bacteria that potentially can cause disease.

Warnings

For external use only. Flammable. Keep away from heat or flame

Do not use

- on open skin wounds
- do not inhale or ingest
- do not use on infants

When using this product keep out of eyes. In case of contact with eyes, flush thoroughly with water

■Avoid contact with open skin ■ Do not inhale or ingest

Stop use and ask a doctor if skin irritation or redness develops.

Keep out of reach of children. If swallowed, get medical help or contact a Poison Control Center right away.

Directions

Wet hands thoroughly with product and allow to dry without wiping
Children under 6 years of age use only under adult supervision
Not recommended for infants

Other information

- Store below 110F (43C)
- May discolor fabrics/surfaces

Inactive ingredients

Aminomethyl Propanol, Ethylmethacrylate, Purified USP Water, Fragrance